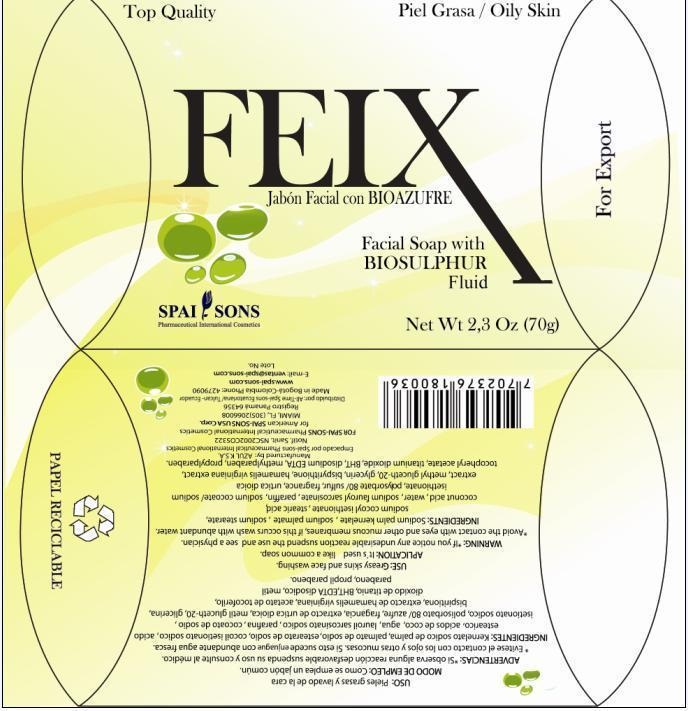 DRUG LABEL: FEIX
NDC: 66854-002 | Form: SOAP
Manufacturer: SPAI-SONS PHAMACEUTICAL INTERNATIONAL COSMETICS
Category: otc | Type: HUMAN OTC DRUG LABEL
Date: 20120425

ACTIVE INGREDIENTS: SULFUR 2 g/100 g
INACTIVE INGREDIENTS: SODIUM PALM KERNELATE; SODIUM PALMITATE; SODIUM STEARATE; SODIUM COCOYL ISETHIONATE; STEARIC ACID; SODIUM SARCOSINATE; PARAFFIN; SODIUM COCOATE; SODIUM ISETHIONATE; POLYSORBATE 80; URTICA DIOICA LEAF; METHYL GLUCETH-20; GLYCERIN; DIPYRITHIONE; HAMAMELIS VIRGINIANA LEAF; .ALPHA.-TOCOPHEROL ACETATE, D-; TITANIUM DIOXIDE; BUTYLATED HYDROXYTOLUENE; EDETATE DISODIUM   ; METHYLPARABEN; PROPYLPARABEN

FEIX JABON FACIAL CON BIOAZUFRE/FACIAL SOAP WITH BIOSULPHUR

ACTIVE INGREDIENT

Feix solid soap, made with coconut fatty esters and sulfur bio-fluid for washing oily skin,or acne-like hyper-secretory.

PURPOSE

Feix solid soap is ideal for washing the skin with rashes, or very sensitive to alkali and soaps made with high concentrations of lye (caustic soda).

KEEP OUT OF REACH OF CHILDREN

This product must be keep out reach of the children.

INDICATIONS AND USAGE

This product is indicated for people who have hypersecretion of fat in the skin. It is used as a regular soap bar with the variety that this soap removes impurities from skin oils.

WARNINGS

Feix, does not irritate or dry skin, is well tolerated at any age.

DOSAGE AND ADMINISTRATION

Feix biosuphur is topical application, rub the soap on the area to be treated gently massaging foam is generated.

INACTIVE INGREDIENT

This soap is made from a series of the ester type excipients that allow proper formation of soap, besides having ingredients that provide moisture to the skin.

IMAGE OF THE CARTON LABEL